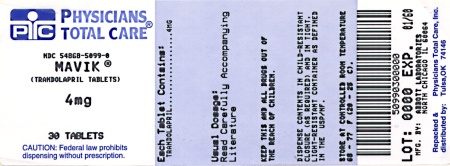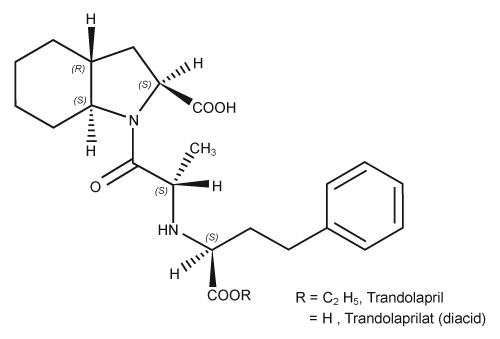 DRUG LABEL: Mavik
NDC: 54868-5099 | Form: TABLET
Manufacturer: Physicians Total Care, Inc.
Category: prescription | Type: HUMAN PRESCRIPTION DRUG LABEL
Date: 20120214

ACTIVE INGREDIENTS: TRANDOLAPRIL 4 mg/1 1
INACTIVE INGREDIENTS: STARCH, CORN; CROSCARMELLOSE SODIUM; LACTOSE; POVIDONE; SODIUM STEARYL FUMARATE; FERRIC OXIDE RED; FERRIC OXIDE YELLOW; HYPROMELLOSES

MAVIK®
(trandolapril tablets)

WARNING: FETAL TOXICITY

- When pregnancy is detected, discontinue MAVIK as soon as possible.
- Drugs that act directly on the renin-angiotensin system can cause injury and death to the developing fetus (See WARNINGS: Fetal Toxicity).

DESCRIPTION

Trandolapril is the ethyl ester prodrug of a nonsulfhydryl angiotensin converting enzyme (ACE) inhibitor, trandolaprilat. Trandolapril is chemically described as (2S, 3aR, 7aS)-1-[(S)-N-[(S)-1-Carboxy-3-phenylpropyl]alanyl] hexahydro-2-indolinecarboxylic acid, 1-ethyl ester. Its empirical formula is C24H34N2O5 and its structural formula is

M.W. = 430.54

Melting Point = 125°C

Trandolapril is a white or almost white powder that is soluble (> 100 mg/mL) in chloroform, dichloromethane, and methanol. MAVIK tablets contain 1 mg, 2 mg, or 4 mg of trandolapril for oral administration. Each tablet also contains corn starch, croscarmellose sodium, hypromellose, iron oxide, lactose monohydrate, povidone, sodium stearyl fumarate.

CLINICAL PHARMACOLOGY

Mechanism of Action

Trandolapril is deesterified to the diacid metabolite, trandolaprilat, which is approximately eight times more active as an inhibitor of ACE activity. ACE is a peptidyl dipeptidase that catalyzes the conversion of angiotensin I to the vasoconstrictor, angiotensin II. Angiotensin II is a potent peripheral vasoconstrictor that also stimulates secretion of aldosterone by the adrenal cortex and provides negative feedback for renin secretion. The effect of trandolapril in hypertension appears to result primarily from the inhibition of circulating and tissue ACE activity thereby reducing angiotensin II formation, decreasing vasoconstriction, decreasing aldosterone secretion, and increasing plasma renin. Decreased aldosterone secretion leads to diuresis, natriuresis, and a small increase of serum potassium. In controlled clinical trials, treatment with MAVIK alone resulted in mean increases in potassium of 0.1 mEq/L. (see PRECAUTIONS.)

ACE is identical to kininase II, an enzyme that degrades bradykinin, a potent peptide vasodilator; whether increased levels of bradykinin play a role in the therapeutic effect of trandolapril remains to be elucidated.

While the principal mechanism of antihypertensive effect is thought to be through the renin-angiotensin-aldosterone system, trandolapril exerts antihypertensive actions even in patients with low-renin hypertension. MAVIK was an effective antihypertensive in all races studied. Both black patients (usually a predominantly low-renin group) and non-black patients responded to 2 to 4 mg of MAVIK.

Pharmacokinetics and Metabolism

Pharmacokinetics

Trandolapril's ACE-inhibiting activity is primarily due to its diacid metabolite, trandolaprilat. Cleavage of the ester group of trandolapril, primarily in the liver, is responsible for conversion. Absolute bioavailability after oral administration of trandolapril is about 10% as trandolapril and 70% as trandolaprilat. After oral trandolapril under fasting conditions, peak trandolapril levels occur at about one hour and peak trandolaprilat levels occur between 4 and 10 hours. The elimination half-life of trandolapril is about 6 hours. At steady state, the effective half-life of trandolaprilat is 22.5 hours. Like all ACE inhibitors, trandolaprilat also has a prolonged terminal elimination phase, involving a small fraction of administered drug, probably representing binding to plasma and tissue ACE. During multiple dosing of trandolapril, there is no significant accumulation of trandolaprilat. Food slows absorption of trandolapril, but does not affect AUC or Cmax of trandolaprilat or Cmax of trandolapril.

Metabolism and Excretion

After oral administration of trandolapril, about 33% of parent drug and metabolites are recovered in urine, mostly as trandolaprilat, with about 66% in feces. The extent of the absorbed dose which is biliary excreted has not been determined. Plasma concentrations (Cmax and AUC of trandolapril and Cmax of trandolaprilat) are dose proportional over the 1-4 mg range, but the AUC of trandolaprilat is somewhat less than dose proportional. In addition to trandolaprilat, at least 7 other metabolites have been found, principally glucuronides or deesterification products.

Serum protein binding of trandolapril is about 80%, and is independent of concentration. Binding of trandolaprilat is concentration-dependent, varying from 65% at 1000 ng/mL to 94% at 0.1 ng/mL, indicating saturation of binding with increasing concentration.

The volume of distribution of trandolapril is about 18 liters. Total plasma clearances of trandolapril and trandolaprilat after approximately 2 mg IV doses are about 52 liters/hour and 7 liters/hour respectively. Renal clearance of trandolaprilat varies from 1-4 liters/hour, depending on dose.

Special Populations

Pediatric

Trandolapril pharmacokinetics have not been evaluated in patients < 18 years of age.

Geriatric and Gender

Trandolapril pharmacokinetics have been investigated in the elderly (> 65 years) and in both genders. The plasma concentration of trandolapril is increased in elderly hypertensive patients, but the plasma concentration of trandolaprilat and inhibition of ACE activity are similar in elderly and young hypertensive patients. The pharmacokinetics of trandolapril and trandolaprilat and inhibition of ACE activity are similar in male and female elderly hypertensive patients.

Race

Pharmacokinetic differences have not been evaluated in different races.

Renal Insufficiency

Compared to normal subjects, the plasma concentrations of trandolapril and trandolaprilat are approximately 2-fold greater and renal clearance is reduced by about 85% in patients with creatinine clearance below 30 ml/min and in patients on hemodialysis. Dosage adjustment is recommended in renally impaired patients. (see DOSAGE AND ADMINISTRATION.)

Hepatic Insufficiency

Following oral administration in patients with mild to moderate alcoholic cirrhosis, plasma concentrations of trandolapril and trandolaprilat were, respectively, 9-fold and 2-fold greater than in normal subjects, but inhibition of ACE activity was not affected. Lower doses should be considered in patients with hepatic insufficiency. (see DOSAGE AND ADMINISTRATION.)

Drug Interactions

Trandolapril did not affect the plasma concentration (pre-dose and 2 hours post-dose) of oral digoxin (0.25 mg). Coadministration of trandolapril and cimetidine led to an increase of about 44% in Cmax for trandolapril, but no difference in the pharmacokinetics of trandolaprilat or in ACE inhibition. Coadministration of trandolapril and furosemide led to an increase of about 25% in the renal clearance of trandolaprilat, but no effect was seen on the pharmacokinetics of furosemide or trandolaprilat or on ACE inhibition.

Pharmacodynamics and Clinical Effects

A single 2-mg dose of MAVIK produces 70 to 85% inhibition of plasma ACE activity at 4 hours with about 10% decline at 24 hours and about half the effect manifest at 8 days. Maximum ACE inhibition is achieved with a plasma trandolaprilat concentration of 2 ng/mL. ACE inhibition is a function of trandolaprilat concentration, not trandolapril concentration. The effect of trandolapril on exogenous angiotensin I was not measured.

Hypertension

Four placebo-controlled dose response studies were conducted using once-daily oral dosing of MAVIK in doses from 0.25 to 16 mg per day in 827 black and non-black patients with mild to moderate hypertension. The minimal effective once-daily dose was 1 mg in non-black patients and 2 mg in black patients. Further decreases in trough supine diastolic blood pressure were obtained in non-black patients with higher doses, and no further response was seen with doses above 4 mg (up to 16 mg). The antihypertensive effect diminished somewhat at the end of the dosing interval, but trough/peak ratios are well above 50% for all effective doses. There was a slightly greater effect on the diastolic pressure, but no difference on systolic pressure with b.i.d. dosing. During chronic therapy, the maximum reduction in blood pressure with any dose is achieved within one week. Following 6 weeks of monotherapy in placebo-controlled trials in patients with mild to moderate hypertension, once-daily doses of 2 to 4 mg lowered supine or standing systolic/diastolic blood pressure 24 hours after dosing by an average 7-10/4-5 mmHg below placebo responses in non-black patients. Once-daily doses of 2 to 4 mg lowered blood pressure 4-6/3-4 mmHg in black patients. Trough to peak ratios for effective doses ranged from 0.5 to 0.9. There were no differences in response between men and women, but responses were somewhat greater in patients under 60 than in patients over 60 years old. Abrupt withdrawal of MAVIK has not been associated with a rapid increase in blood pressure.

Administration of MAVIK to patients with mild to moderate hypertension results in a reduction of supine, sitting and standing blood pressure to about the same extent without compensatory tachycardia.

Symptomatic hypotension is infrequent, although it can occur in patients who are salt- and/or volume-depleted. (see WARNINGS.) Use of MAVIK in combination with thiazide diuretics gives a blood pressure lowering effect greater than that seen with either agent alone, and the additional effect of trandolapril is similar to the effect of monotherapy.

Heart Failure Post Myocardial Infarction or Left Ventricular Dysfunction Post Myocardial Infarction

The Trandolapril Cardiac Evaluation (TRACE) Trial was a Danish, 27-center, double-blind, placebo controlled, parallel-group study of the effect of trandolapril on all-cause mortality in stable patients with echocardiographic evidence of left ventricular dysfunction 3 to 7 days after a myocardial infarction. Subjects with residual ischemia or overt heart failure were included. Patients tolerant of a test dose of 1 mg trandolapril were randomized to placebo (n=873) or trandolapril (n=876) and followed for 24 months. Among patients randomized to trandolapril, who began treatment on 1 mg, 62% were successfully titrated to a target dose of 4 mg once daily over a period of weeks. The use of trandolapril was associated with a 16% reduction in the risk of all-cause mortality (p=0.042), largely cardiovascular mortality. Trandolapril was also associated with a 20% reduction in the risk of progression of heart failure (p=0.047), defined by a time-to-first-event analysis of death attributed to heart failure, hospitalization for heart failure, or requirement for open-label ACE inhibitor for the treatment of heart failure. There was no significant effect of treatment on other end-points: subsequent hospitalization, incidence of recurrent myocardial infarction, exercise tolerance, ventricular function, ventricular dimensions, or NYHA class.

The population in TRACE was entirely Caucasian and had less usage than would be typical in a U.S. population of other post-infarction interventions: 42% thrombolysis, 16% beta-adrenergic blockade, and 6.7% PTCA or CABG during the entire period of follow-up. Blood pressure control, especially in the placebo group, was poor: 47 to 53% of patients randomized to placebo and 32 to 40% of patients randomized to trandolapril had blood pressures > 140/95 at 90-day follow-up visits.

INDICATIONS AND USAGE

Hypertension

MAVIK is indicated for the treatment of hypertension. It may be used alone or in combination with other antihypertensive medication such as hydrochlorothiazide.

Heart Failure Post Myocardial Infarction or Left-Ventricular Dysfunction Post Myocardial Infarction

MAVIK is indicated in stable patients who have evidence of left-ventricular systolic dysfunction (identified by wall motion abnormalities) or who are symptomatic from congestive heart failure within the first few days after sustaining acute myocardial infarction. Administration of trandolapril to Caucasian patients has been shown to decrease the risk of death (principally cardiovascular death) and to decrease the risk of heart failure-related hospitalization (see CLINICAL PHARMACOLOGY - Heart Failure or Left-Ventricular Dysfunction Post Myocardial Infarction for details of the survival trial).

CONTRAINDICATIONS

MAVIK is contraindicated in patients who are hypersensitive to this product, in patients with hereditary/idiopathic angioedema and in patients with a history of angioedema related to previous treatment with an ACE inhibitor.

WARNINGS

Anaphylactoid and Possibly Related Reactions

Presumably because angiotensin converting enzyme inhibitors affect the metabolism of eicosanoids and polypeptides, including endogenous bradykinin, patients receiving ACE inhibitors, including MAVIK, may be subject to a variety of adverse reactions, some of them serious.

Anaphylactoid Reactions During Desensitization

Two patients undergoing desensitizing treatment with hymenoptera venom while receiving ACE inhibitors sustained life-threatening anaphylactoid reactions. In the same patients, these reactions did not occur when ACE inhibitors were temporarily withheld, but they reappeared when the ACE inhibitors were inadvertently readministered.

Anaphylactoid Reactions During Membrane Exposure

Anaphylactoid reactions have been reported in patients dialyzed with high-flux membranes and treated concomitantly with an ACE inhibitor. Anaphylactoid reactions have also been reported in patients undergoing low-density lipoprotein apheresis with dextran sulfate absorption.

Head and Neck Angioedema

In controlled trials ACE inhibitors (for which adequate data are available) cause a higher rate of angioedema in black than in non-black patients.

Angioedema of the face, extremities, lips, tongue, glottis, and larynx has been reported in patients treated with ACE inhibitors including MAVIK. Symptoms suggestive of angioedema or facial edema occurred in 0.13% of MAVIK-treated patients. Two of the four cases were life-threatening and resolved without treatment or with medication (corticosteroids). Angioedema associated with laryngeal edema can be fatal. If laryngeal stridor or angioedema of the face, tongue or glottis occurs, treatment with MAVIK should be discontinued immediately, the patient treated in accordance with accepted medical care and carefully observed until the swelling disappears. In instances where swelling is confined to the face and lips, the condition generally resolves without treatment; antihistamines may be useful in relieving symptoms. Where there is involvement of the tongue, glottis, or larynx, likely to cause airway obstruction, emergency therapy, including but not limited to subcutaneous epinephrine solution 1:1,000 (0.3 to 0.5 mL) should be promptly administered. (see PRECAUTIONS - Information for Patients and ADVERSE REACTIONS.)

Intestinal Angioedema

Intestinal angioedema has been reported in patients treated with ACE inhibitors. These patients presented with abdominal pain (with or without nausea or vomiting); in some cases there was no prior history of facial angioedema and C-1 esterase levels were normal. The angioedema was diagnosed by procedures including abdominal CT scan or ultrasound, or at surgery, and symptoms resolved after stopping the ACE inhibitor. Intestinal angioedema should be included in the differential diagnosis of patients on ACE inhibitors presenting with abdominal pain.

Hypotension

MAVIK can cause symptomatic hypotension. Like other ACE inhibitors, MAVIK has only rarely been associated with symptomatic hypotension in uncomplicated hypertensive patients. Symptomatic hypotension is most likely to occur in patients who have been salt- or volume-depleted as a result of prolonged treatment with diuretics, dietary salt restriction, dialysis, diarrhea, or vomiting. Volume and/or salt depletion should be corrected before initiating treatment with MAVIK. (see PRECAUTIONS - Drug Interactions and ADVERSE REACTIONS.) In controlled and uncontrolled studies, hypotension was reported as an adverse event in 0.6% of patients and led to discontinuations in 0.1% of patients.

In patients with concomitant congestive heart failure, with or without associated renal insufficiency, ACE inhibitor therapy may cause excessive hypotension, which may be associated with oliguria or azotemia, and rarely, with acute renal failure and death. In such patients, MAVIK therapy should be started at the recommended dose under close medical supervision. These patients should be followed closely during the first 2 weeks of treatment and, thereafter, whenever the dosage of MAVIK or diuretic is increased. (see DOSAGE AND ADMINISTRATION.) Care in avoiding hypotension should also be taken in patients with ischemic heart disease, aortic stenosis, or cerebrovascular disease.

If symptomatic hypotension occurs, the patient should be placed in the supine position and, if necessary, normal saline may be administered intravenously. A transient hypotensive response is not a contraindication to further doses; however, lower doses of MAVIK or reduced concomitant diuretic therapy should be considered.

Neutropenia/Agranulocytosis

Another ACE inhibitor, captopril, has been shown to cause agranulocytosis and bone marrow depression rarely in patients with uncomplicated hypertension, but more frequently in patients with renal impairment, especially if they also have a collagen-vascular disease such as systemic lupus erythematosus or scleroderma. Available data from clinical trials of trandolapril are insufficient to show that trandolapril does not cause agranulocytosis at similar rates. As with other ACE inhibitors, periodic monitoring of white blood cell counts in patients with collagen-vascular disease and/or renal disease should be considered.

Hepatic Failure

ACE inhibitors rarely have been associated with a syndrome of cholestatic jaundice, fulminant hepatic necrosis, and death. The mechanism of this syndrome is not understood. Patients receiving ACE inhibitors who develop jaundice should discontinue the ACE inhibitor and receive appropriate medical follow-up.

Fetal Toxicity

Pregnancy Category D

Use of drugs that act on the renin-angiotensin system during the second and third trimesters of pregnancy reduces fetal renal function and increases fetal and neonatal morbidity and death. Resulting oligohydramnios can be associated with fetal lung hypoplasia and skeletal deformations. Potential neonatal adverse effects include skull hypoplasia, anuria, hypotension, renal failure, and death. When pregnancy is detected, discontinue MAVIK as soon as possible. These adverse outcomes are usually associated with use of these drugs in the second and third trimester of pregnancy. Most epidemiologic studies examining fetal abnormalities after exposure to antihypertensive use in the first trimester have not distinguished drugs affecting the renin-angiotensin system from other antihypertensive agents. Appropriate management of maternal hypertension during pregnancy is important to optimize outcomes for both mother and fetus.

In the unusual case that there is no appropriate alternative to therapy with drugs affecting the renin-angiotensin system for a particular patient, apprise the mother of the potential risk to the fetus. Perform serial ultrasound examinations to assess the intra-amniotic environment. If oligohydramnios is observed, discontinue MAVIK, unless it is considered lifesaving for the mother. Fetal testing may be appropriate, based on the week of pregnancy. Patients and physicians should be aware, however, that oligohydramnios may not appear until after the fetus has sustained irreversible injury. Closely observe infants with histories of in utero exposure to MAVIK for hypotension, oliguria, and hyperkalemia (See PRECAUTIONS, Pediatric Use).

Doses of 0.8 mg/kg/day (9.4 mg/m2/day) in rabbits, 1000 mg/kg/day (7000 mg/m2/day) in rats, and 25 mg/kg/day (295 mg/m2/day) in cynomolgus monkeys did not produce teratogenic effects. These doses represent 10 and 3 times (rabbits), 1250 and 2564 times (rats), and 312 and 108 times (monkeys) the maximum projected human dose of 4 mg based on body-weight and body-surface-area, respectively assuming a 50 kg woman.

PRECAUTIONS

General

Impaired Renal Function

As a consequence of inhibiting the renin-angiotensin-aldosterone system, changes in renal function may be anticipated in susceptible individuals. In patients with severe heart failure whose renal function may depend on the activity of the renin-angiotensin-aldosterone system, treatment with ACE inhibitors, including MAVIK (trandolapril), may be associated with oliguria and/or progressive azotemia and rarely with acute renal failure and/or death.

In hypertensive patients with unilateral or bilateral renal artery stenosis, increases in blood urea nitrogen and serum creatinine have been observed in some patients following ACE inhibitor therapy. These increases were almost always reversible upon discontinuation of the ACE inhibitor and/or diuretic therapy. In such patients, renal function should be monitored during the first few weeks of therapy.

Some hypertensive patients with no apparent preexisting renal vascular disease have developed increases in blood urea and serum creatinine, usually minor and transient, especially when ACE inhibitors have been given concomitantly with a diuretic. This is more likely to occur in patients with preexisting renal impairment. Dosage reduction and/or discontinuation of any diuretic and/or the ACE inhibitor may be required. Evaluation of hypertensive patients should always include assessment of renal function. (see DOSAGE AND ADMINISTRATION.)

Hyperkalemia and Potassium-sparing Diuretics

In clinical trials, hyperkalemia (serum potassium > 6.00 mEq/L) occurred in approximately 0.4% of hypertensive patients receiving MAVIK. In most cases, elevated serum potassium levels were isolated values, which resolved despite continued therapy. None of these patients were discontinued from the trials because of hyperkalemia. Risk factors for the development of hyperkalemia include renal insufficiency, diabetes mellitus, and the concomitant use of potassium-sparing diuretics, potassium supplements, and/or potassium-containing salt substitutes, which should be used cautiously, if at all, with MAVIK. (see PRECAUTIONS - Drug Interactions.)

Cough

Presumably due to the inhibition of the degradation of endogenous bradykinin, persistent nonproductive cough has been reported with all ACE inhibitors, always resolving after discontinuation of therapy. ACE inhibitor-induced cough should be considered in the differential diagnosis of cough. In controlled trials of trandolapril, cough was present in 2% of trandolapril patients and 0% of patients given placebo. There was no evidence of a relationship to dose.

Surgery/Anesthesia

In patients undergoing major surgery or during anesthesia with agents that produce hypotension, MAVIK will block angiotensin II formation secondary to compensatory renin release. If hypotension occurs and is considered to be due to this mechanism, it can be corrected by volume expansion.

Information for Patients

Angioedema

Angioedema, including laryngeal edema, may occur at any time during treatment with ACE inhibitors, including MAVIK. Patients should be so advised and told to report immediately any signs or symptoms suggesting angioedema (swelling of face, extremities, eyes, lips, tongue, difficulty in swallowing or breathing) and to stop taking the drug until they have consulted with their physician. (see WARNINGS and ADVERSE REACTIONS.)

Symptomatic Hypotension

Patients should be cautioned that light-headedness can occur, especially during the first days of MAVIK therapy, and should be reported to a physician. If actual syncope occurs, patients should be told to stop taking the drug until they have consulted with their physician (see WARNINGS).

All patients should be cautioned that inadequate fluid intake, excessive perspiration, diarrhea, or vomiting, resulting in reduced fluid volume, may precipitate an excessive fall in blood pressure with the same consequences of light-headedness and possible syncope.

Patients planning to undergo any surgery and/or anesthesia should be told to inform their physician that they are taking an ACE inhibitor that has a long duration of action.

Hyperkalemia

Patients should be told not to use potassium supplements or salt substitutes containing potassium without consulting their physician. (see PRECAUTIONS.)

Neutropenia

Patients should be told to report promptly any indication of infection (e.g., sore throat, fever) which could be a sign of neutropenia.

Pregnancy

Female patients of childbearing age should be told about the consequences of exposure to MAVIK during pregnancy. Discuss treatment options with women planning to become pregnant. Patients should be asked to report pregnancies to their physicians as soon as possible.

NOTE: As with many other drugs, certain advice to patients being treated with MAVIK is warranted. This information is intended to aid in the safe and effective use of this medication. It is not a disclosure of all possible adverse or intended effects.

Drug Interactions

Concomitant Diuretic Therapy

As with other ACE inhibitors, patients on diuretics, especially those on recently instituted diuretic therapy, may experience an excessive reduction of blood pressure after initiation of therapy with MAVIK. The possibility of exacerbation of hypotensive effects with MAVIK may be minimized by either discontinuing the diuretic or cautiously increasing salt intake prior to initiation of treatment with MAVIK. If it is not possible to discontinue the diuretic, the starting dose of trandolapril should be reduced. (see DOSAGE AND ADMINISTRATION.)

Agents Increasing Serum Potassium

Trandolapril can attenuate potassium loss caused by thiazide diuretics and increase serum potassium when used alone. Use of potassium-sparing diuretics (spironolactone, triamterene, or amiloride), potassium supplements, or potassium-containing salt substitutes concomitantly with ACE inhibitors can increase the risk of hyperkalemia. If concomitant use of such agents is indicated, they should be used with caution and with appropriate monitoring of serum potassium. (see PRECAUTIONS.)

Antidiabetic Agents

Concomitant use of ACE inhibitors and antidiabetic medicines (insulin or oral hypoglycemic agents) may cause an increased blood glucose lowering effect with greater risk of hypoglycemia.

Lithium

Increased serum lithium levels and symptoms of lithium toxicity have been reported in patients receiving concomitant lithium and ACE inhibitor therapy. These drugs should be coadministered with caution, and frequent monitoring of serum lithium levels is recommended. If a diuretic is also used, the risk of lithium toxicity may be increased.

Non-Steroidal Anti-Inflammatory Agents including Selective Cyclooxygenase-2 Inhibitors (COX-2 Inhibitors)

In patients who are elderly, volume-depleted (including those on diuretic therapy), or with compromised renal function, co-administration of NSAIDs, including selective COX-2 inhibitors, with ACE inhibitors, including trandolapril, may result in deterioration of renal function, including possible acute renal failure. These effects are usually reversible. Monitor renal function periodically in patients receiving trandolapril and NSAID therapy.

The antihypertensive effect of ACE inhibitors, including trandolapril may be attenuated by NSAIDs.

Gold

Nitritoid reactions (symptoms include facial flushing, nausea, vomiting and hypotension) have been reported rarely in patients on therapy with injectable gold (sodium aurothiomalate) and concomitant ACE inhibitor therapy including MAVIK.

Other

No clinically significant pharmacokinetic interaction has been found between trandolaprilat and food, cimetidine, digoxin, or furosemide.

The anticoagulant effect of warfarin was not significantly changed by trandolapril.

As with all other inhibitors of RAS, NSAIDs may reduce the antihypertensive effects of trandolapril. Blood pressure monitoring should be increased when any NSAID is added or discontinued in a patient treated with trandolapril.

The hypotensive effect of certain inhalation anesthetics may be enhanced by ACE inhibitors including trandolapril (see PRECAUTIONS-Surgery/Anesthesia).

Carcinogenesis, Mutagenesis, Impairment of Fertility

Long-term studies were conducted with oral trandolapril administered by gavage to mice (78 weeks) and rats (104 and 106 weeks). No evidence of carcinogenic potential was seen in mice dosed up to 25 mg/kg/day (85 mg/m^2/day) or rats dosed up to 8 mg/kg/day (60 mg/m^2/day). These doses are 313 and 32 times (mice), and 100 and 23 times (rats) the maximum recommended human daily dose (MRHDD) of 4 mg based on body-weight and body-surface-area, respectively assuming a 50 kg individual. The genotoxic potential of trandolapril was evaluated in the microbial mutagenicity (Ames) test, the point mutation and chromosome aberration assays in Chinese hamster V79 cells, and the micronucleus test in mice. There was no evidence of mutagenic or clastogenic potential in these in vitro and in vivo assays.

Reproduction studies in rats did not show any impairment of fertility at doses up to 100 mg/kg/day (710 mg/m^2/day) of trandolapril, or 1250 and 260 times the MRHDD on the basis of body-weight and body-surface-area, respectively.

Nursing Mothers

Radiolabeled trandolapril or its metabolites are secreted in rat milk. MAVIK should not be administered to nursing mothers.

Geriatric Use

In placebo-controlled studies of MAVIK, 31.1% of patients were 60 years and older, 20.1% were 65 years and older, and 2.3% were 75 years and older. No overall differences in effectiveness or safety were observed between these patients and younger patients. (Greater sensitivity of some older individual patients cannot be ruled out).

Pediatric Use

Neonates with a history of in utero exposure to MAVIK:

If oliguria or hypotension occurs, direct attention toward support of blood pressure and renal perfusion. Exchange transfusions or dialysis may be required as a means of reversing hypotension and/or substituting for disordered renal function.

The safety and effectiveness of MAVIK in pediatric patients have not been established.

ADVERSE REACTIONS

The safety experience in U.S. placebo-controlled trials included 1069 hypertensive patients, of whom 832 received MAVIK. Nearly 200 hypertensive patients received MAVIK for over one year in open-label trials. In controlled trials, withdrawals for adverse events were 2.1% on placebo and 1.4% on MAVIK. Adverse events considered at least possibly related to treatment occurring in 1% of MAVIK-treated patients and more common on MAVIK than placebo, pooled for all doses, are shown below, together with the frequency of discontinuation of treatment because of these events.

ADVERSE EVENTS IN PLACEBO-CONTROLLED HYPERTENSION TRIALS
 | Occurring at 1% or greater
 | MAVIK (N=832) % Incidence (% Discontinuance) | PLACEBO (N=237) % Incidence (% Discontinuance)
Cough | 1.9 (0.1) | 0.4 (0.4)
Dizziness | 1.3 (0.2) | 0.4 (0.4)
Diarrhea | 1.0 (0.0) | 0.4 (0.0)

Headache and fatigue were all seen in more than 1% of MAVIK-treated patients but were more frequently seen on placebo. Adverse events were not usually persistent or difficult to manage.

Left Ventricular Dysfunction Post Myocardial Infarction

Adverse reactions related to MAVIK occurring at a rate greater than that observed in placebo-treated patients with left ventricular dysfunction, are shown below. The incidences represent the experiences from the TRACE study. The follow-up time was between 24 and 50 months for this study.

Percentage of Patients with Adverse Events Greater Than Placebo
Placebo-Controlled (TRACE)
Mortality Study
Adverse Event | Trandolapril N=876 | Placebo N=873
Cough | 35 | 22
Dizziness | 23 | 17
Hypotension | 11 | 6.8
Elevated serum uric acid | 15 | 13
Elevated BUN | 9.0 | 7.6
PICA or CABG | 7.3 | 6.1
Dyspepsia | 6.4 | 6.0
Syncope | 5.9 | 3.3
Hyperkalemia | 5.3 | 2.8
Bradycardia | 4.7 | 4.4
Hypocalcemia | 4.7 | 3.9
Myalgia | 4.7 | 3.1
Elevated creatinine | 4.7 | 2.4
Gastritis | 4.2 | 3.6
Cardiogenic shock | 3.8 | < 2
Intermittent claudication | 3.8 | < 2
Stroke | 3.3 | 3.2
Asthenia | 3.3 | 2.6

Clinical adverse experiences possibly or probably related or of uncertain relationship to therapy occurring in 0.3% to 1.0% (except as noted) of the patients treated with MAVIK (with or without concomitant calcium ion antagonist or diuretic) in controlled or uncontrolled trials (N=1134) and less frequent, clinically significant events seen in clinical trials or post-marketing experience include (listed by body system):

General Body Function

Chest pain.

Cardiovascular

AV first degree block, bradycardia, edema, flushing, and palpitations.

Central Nervous System

Drowsiness, insomnia, paresthesia, vertigo.

Dermatologic

Pruritus, rash, pemphigus.

Eye, Ear, Nose, Throat

Epistaxis, throat inflammation, upper respiratory tract infection.

Emotional, Mental, Sexual States

Anxiety, impotence, decreased libido.

Gastrointestinal

Abdominal distention, abdominal pain/cramps, constipation, dyspepsia, diarrhea, vomiting, nausea.

Hemopoietic

Decreased leukocytes, decreased neutrophils.

Metabolism and Endocrine

Increased liver enzymes including SGPT (ALT).

Musculoskeletal System

Extremity pain, muscle cramps, gout.

Pulmonary

Dyspnea.

Postmarketing

The following adverse reactions were identified during post approval use of MAVIK. Because these reactions are reported voluntarily from a population of uncertain size, it is not always possible to reliably estimate their frequency or establish a causal relationship to drug exposure.

General Body Function

Malaise, fever.

Cardiovascular

Myocardial infarction, myocardial ischemia, angina pectoris, cardiac failure, ventricular tachycardia, tachycardia, transient ischemic attack, arrhythmia.

Central Nervous System

Cerebral hemorrhage.

Dermatologic

Alopecia, sweating, Stevens-Johnson syndrome and toxic epidermal necrolysis.

Emotional, Mental, Sexual States

Hallucination, depression.

Gastrointestinal

Dry mouth, pancreatitis, jaundice and hepatitis.

Hemopoietic

Agranulocytosis, pancytopenia.

Metabolism and Endocrine

Increased SGOT (AST).

Pulmonary

Bronchitis.

Renal and Urinary

Renal failure.

Clinical Laboratory Test Findings

Hematology

Thrombocytopenia.

Serum Electrolytes

Hyponatremia.

Creatinine and Blood Urea Nitrogen

Increases in creatinine levels occurred in 1.1% of patients receiving MAVIK alone and 7.3% of patients treated with MAVIK, a calcium ion antagonist and a diuretic. Increases in blood urea nitrogen levels occurred in 0.6% of patients receiving MAVIK alone and 1.4% of patients receiving MAVIK, a calcium ion antagonist, and a diuretic. None of these increases required discontinuation of treatment. Increases in these laboratory values are more likely to occur in patients with renal insufficiency or those pretreated with a diuretic and, based on experience with other ACE inhibitors, would be expected to be especially likely in patients with renal artery stenosis. (see PRECAUTIONS and WARNINGS.)

Liver Function Tests

Occasional elevation of transaminases at the rate of 3X upper normals occurred in 0.8% of patients and persistent increase in bilirubin occurred in 0.2% of patients. Discontinuation for elevated liver enzymes occurred in 0.2% of patients.

Other

Another potentially important adverse experience, eosinophilic pneumonitis, has been attributed to other ACE inhibitors.

OVERDOSAGE

No data are available with respect to overdosage in humans. The oral LD50 of trandolapril in mice was 4875 mg/Kg in males and 3990 mg/Kg in females. In rats, an oral dose of 5000 mg/Kg caused low mortality (1 male out of 5; 0 females). In dogs, an oral dose of 1000 mg/Kg did not cause mortality and abnormal clinical signs were not observed. In humans, the most likely clinical manifestation would be symptoms attributable to severe hypotension. Symptoms also expected with ACE inhibitors are hypotension, hyperkalemia, and renal failure.

Laboratory determinations of serum levels of trandolapril and its metabolites are not widely available, and such determinations have, in any event, no established role in the management of trandolapril overdose. No data are available to suggest that physiological maneuvers (e.g., maneuvers to change the pH of the urine) might accelerate elimination of trandolapril and its metabolites. Trandolaprilat is removed by hemodialysis. Angiotensin II could presumably serve as a specific antagonist antidote in the setting of trandolapril overdose, but angiotensin II is essentially unavailable outside of scattered research facilities. Because the hypotensive effect of trandolapril is achieved through vasodilation and effective hypovolemia, it is reasonable to treat trandolapril overdose by infusion of normal saline solution.

DOSAGE AND ADMINISTRATION

Hypertension

The recommended initial dosage of MAVIK for patients not receiving a diuretic is 1 mg once daily in non-black patients and 2 mg in black patients. Dosage should be adjusted according to the blood pressure response. Generally, dosage adjustments should be made at intervals of at least 1 week. Most patients have required dosages of 2 to 4 mg once daily. There is little clinical experience with doses above 8 mg.

Patients inadequately treated with once-daily dosing at 4 mg may be treated with twice-daily dosing. If blood pressure is not adequately controlled with MAVIK monotherapy, a diuretic may be added.

In patients who are currently being treated with a diuretic, symptomatic hypotension occasionally can occur following the initial dose of MAVIK. To reduce the likelihood of hypotension, the diuretic should, if possible, be discontinued two to three days prior to beginning therapy with MAVIK. (see WARNINGS.) Then, if blood pressure is not controlled with MAVIK alone, diuretic therapy should be resumed. If the diuretic cannot be discontinued, an initial dose of 0.5 mg MAVIK should be used with careful medical supervision for several hours until blood pressure has stabilized. The dosage should subsequently be titrated (as described above) to the optimal response. (see WARNINGS, PRECAUTIONS and DRUG INTERACTIONS.)

Concomitant administration of MAVIK with potassium supplements, potassium salt substitutes, or potassium sparing diuretics can lead to increases of serum potassium. (see PRECAUTIONS.)

Heart Failure Post Myocardial Infarction or Left-Ventricular Dysfunction Post Myocardial Infarction

The recommended starting dose is 1 mg, once daily. Following the initial dose, all patients should be titrated (as tolerated) toward a target dose of 4 mg, once daily. If a 4 mg dose is not tolerated, patients can continue therapy with the greatest tolerated dose.

Dosage Adjustment in Renal Impairment or Hepatic Cirrhosis

For patients with a creatinine clearance < 30 mL/min. or with hepatic cirrhosis, the recommended starting dose, based on clinical and pharmacokinetic data, is 0.5 mg daily. Patients should subsequently have their dosage titrated (as described above) to the optimal response.

HOW SUPPLIED

MAVIK (trandolapril tablets) are supplied as follows:

4 mg tablet - Rose colored, round shaped, compressed tablets, with Abbott “A” logo on one side and Abbo-Code identification letters FZ on the other side.

Bottles of 10 | NDC 54868-5099-1
Bottles of 30 | NDC 54868-5099-0

Dispense in well-closed container with safety closure.

Storage

Store at controlled room temperature: 20-25°C (68-77°F) see USP.

Manufactured by

Halo Pharmaceutical Inc.

Whippany, N.J. 07981, U.S.A.

for

Abbott Laboratories

North Chicago, IL 60064, U.S.A.

Revised: 1/2012

Relabeling and Repackaging by:
Physicians Total Care, Inc.
Tulsa, Oklahoma 74146

PRINCIPAL DISPLAY PANEL

MAVIK® 4mg (trandolapril) Tablets

Do not accept if seal over bottle opening is broken or missing.

Rx only